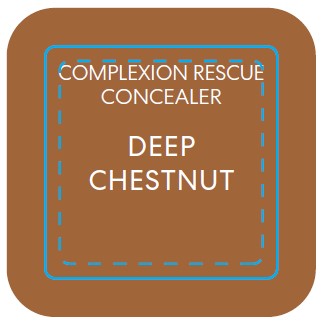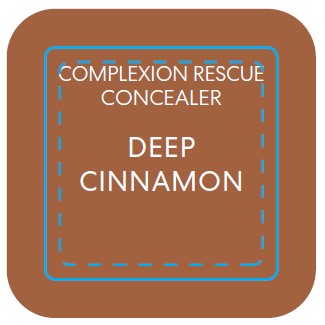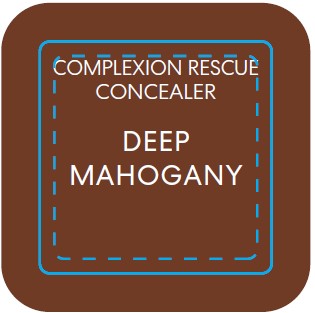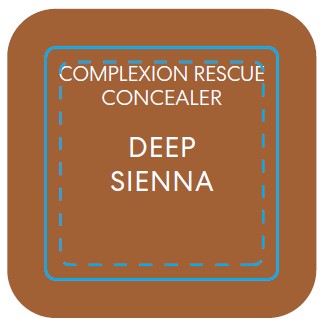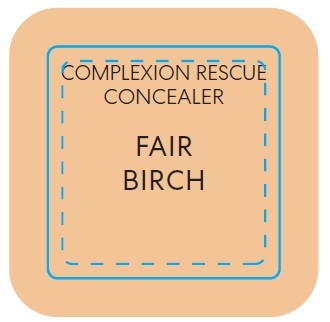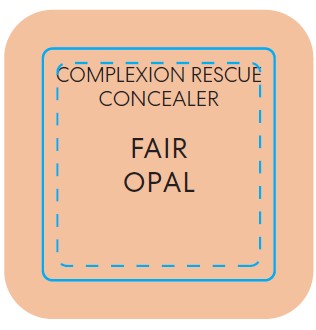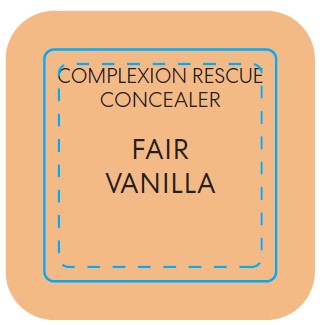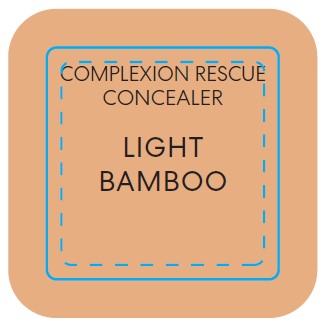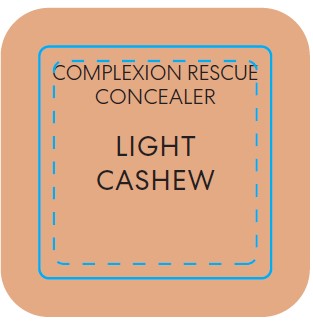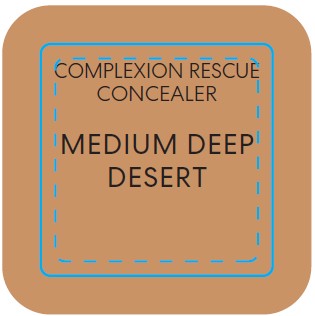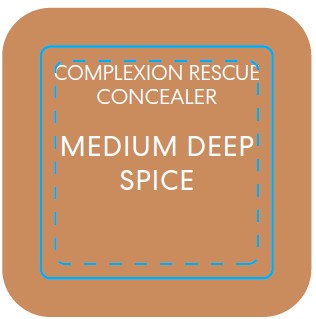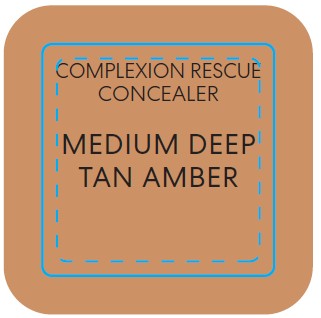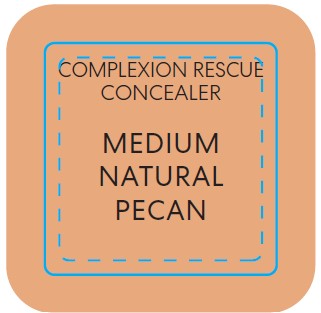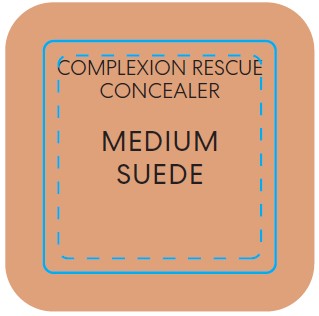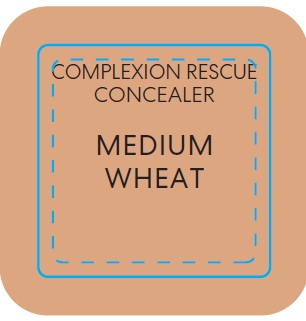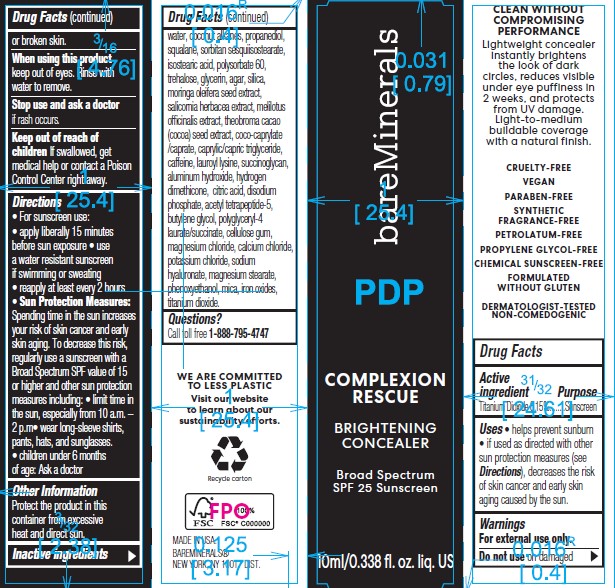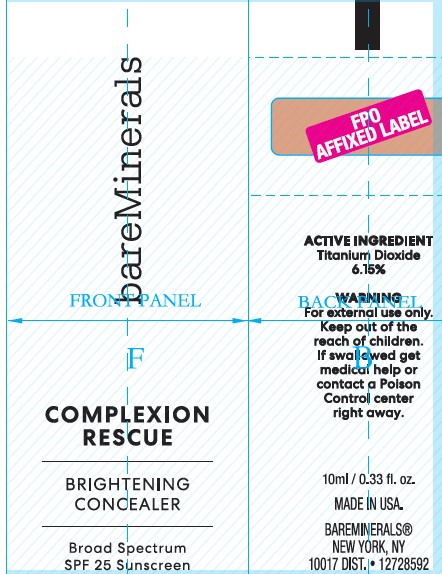 DRUG LABEL: bareMinerals Complexion Rescue Brightening Concealer SPF 25
NDC: 98132-284 | Form: LIQUID
Manufacturer: Orveon Global US LLC
Category: otc | Type: HUMAN OTC DRUG LABEL
Date: 20231004

ACTIVE INGREDIENTS: TITANIUM DIOXIDE 0.065 g/10 mL
INACTIVE INGREDIENTS: PROPANEDIOL; ISOSTEARIC ACID; POLYSORBATE 60; GLYCERIN; SILICON DIOXIDE; MORINGA OLEIFERA SEED; SALICORNIA EUROPAEA WHOLE; COCO-CAPRYLATE/CAPRATE; LAUROYL LYSINE; ACETYL TETRAPEPTIDE-5; POLYGLYCERYL-4 LAURATE/SUCCINATE; CARBOXYMETHYLCELLULOSE SODIUM, UNSPECIFIED; MAGNESIUM CHLORIDE; POTASSIUM CHLORIDE; HYALURONATE SODIUM; MAGNESIUM STEARATE; PHENOXYETHANOL; MICA; FERROUS OXIDE; MEDIUM-CHAIN TRIGLYCERIDES; HYDROGEN DIMETHICONE (13 CST); WATER; COCONUT ALKANES; SQUALANE; CAFFEINE; ALUMINUM HYDROXIDE; CALCIUM CHLORIDE; CITRIC ACID MONOHYDRATE; SODIUM PHOSPHATE, DIBASIC, ANHYDROUS; MELILOTUS OFFICINALIS WHOLE; COCOA; TREHALOSE; SORBITAN SESQUIISOSTEARATE; AGAR; BUTYLENE GLYCOL

bareMinerals Complexion Rescue Brightening Concealer SPF 25

Uses

- Helps prevent sunburn.

Warnings

For external use only.

Directions

- Apply liberally 15 minutes before sun exposure
- Reapply at least every 2 hours
- Use a water resistant sunscreen if swimming or sweating
- Children under 6 months of age: ask a doctor

Inactive ingredients

WATER, COCONUT ALKANES, PROPANEDIOL, SQUALANE, SORBITAN SESQUIISOSTEARATE, ISOSTEARIC ACID, POLYSORBATE 60, TREHALOSE, GLYCERIN, AGAR, SILICA, MORINGA OLEIFERA SEED EXTRACT, SALICORNIA HERBACEA EXTRACT, MELILOTUS OFFICINALIS EXTRACT, THEOBROMA CACAO (COCOA) SEED EXTRACT, COCO-CAPRYLATE /CAPRATE, CAPRYLIC/CAPRIC TRIGLYCERIDE, CAFFEINE, LAUROYL LYSINE, SUCCINOGLYCAN, ALUMINUM
HYDROXIDE, HYDROGEN DIMETHICONE, CITRIC ACID, DISODIUM PHOSPHATE, ACETYL TETRAPEPTIDE-5, BUTYLENE
GLYCOL, POLYGLYCERYL-4 LAURATE/SUCCINATE, CELLULOSE GUM, MAGNESIUM CHLORIDE, CALCIUM CHLORIDE, POTASSIUM CHLORIDE, SODIUM HYALURONATE, MAGNESIUM STEARATE, PHENOXYETHANOL, MICA, IRON OXIDES, TITANIUM DIOXIDE.

Other information

- Protect the product in this container from excessive heat and direct sun.

Principal Display Panel - 10 mL / 0.338 fl. oz. liq. US

bareMinerals Complexion Rescue Brightening Concealer SPF 25

Fair Opal

Principal Display Panel - 10 mL / 0.338 fl. oz. liq. US

bareMinerals Complexion Rescue Brightening Concealer SPF 25

Fair Vanilla

Principal Display Panel - 10 mL / 0.338 fl. oz. liq. US

bareMinerals Complexion Rescue Brightening Concealer SPF 25

Fair Birch

Principal Display Panel - 10 mL / 0.338 fl. oz. liq. US

bareMinerals Complexion Rescue Brightening Concealer SPF 25

Light Cashew

Principal Display Panel - 10 mL / 0.338 fl. oz. liq. US

bareMinerals Complexion Rescue Brightening Concealer SPF 25

Light Bamboo

Principal Display Panel - 10 mL / 0.338 fl. oz. liq. US

bareMinerals Complexion Rescue Brightening Concealer SPF 25

Medium Wheat

Principal Display Panel - 10 mL / 0.338 fl. oz. liq. US

bareMinerals Complexion Rescue Brightening Concealer SPF 25

Medium Suede

Principal Display Panel - 10 mL / 0.338 fl. oz. liq. US

bareMinerals Complexion Rescue Brightening Concealer SPF 25

Medium Natural Pecan

Principal Display Panel - 10 mL / 0.338 fl. oz. liq. US

bareMinerals Complexion Rescue Brightening Concealer SPF 25

Medium Deep Tan Amber

Principal Display Panel - 10 mL / 0.338 fl. oz. liq. US

bareMinerals Complexion Rescue Brightening Concealer SPF 25

Medium Deep Desert

Principal Display Panel - 10 mL / 0.338 fl. oz. liq. US

bareMinerals Complexion Rescue Brightening Concealer SPF 25

Medium Deep Spice

Principal Display Panel - 10 mL / 0.338 fl. oz. liq. US

bareMinerals Complexion Rescue Brightening Concealer SPF 25

Deep Chestnut

Principal Display Panel - 10 mL / 0.338 fl. oz. liq. US

bareMinerals Complexion Rescue Brightening Concealer SPF 25

Deep Sienna

Principal Display Panel - 10 mL / 0.338 fl. oz. liq. US

bareMinerals Complexion Rescue Brightening Concealer SPF 25

Deep Cinnamon

Principal Display Panel - 10 mL / 0.338 fl. oz. liq. US

bareMinerals Complexion Rescue Brightening Concealer SPF 25

Deep Mahogany